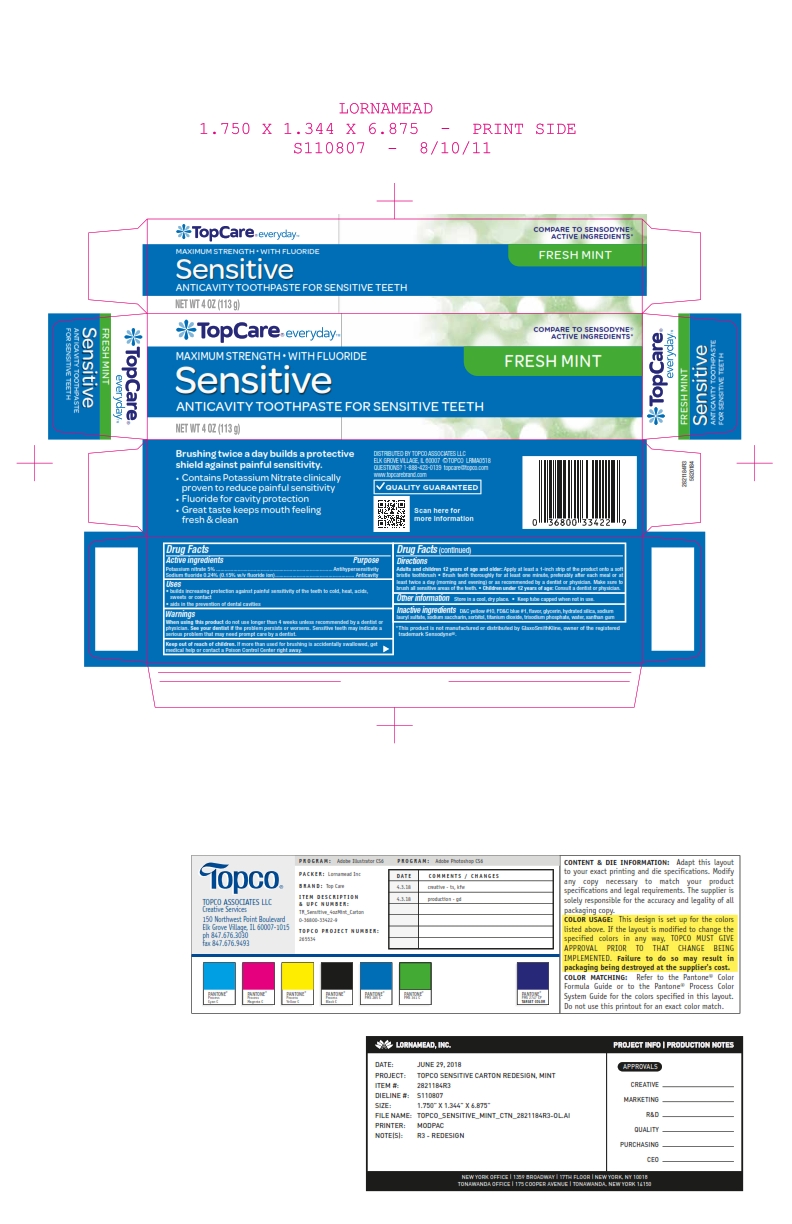 DRUG LABEL: Topco Associates LLC
NDC: 36800-481 | Form: PASTE, DENTIFRICE
Manufacturer: Topco Associates LLC
Category: otc | Type: HUMAN OTC DRUG LABEL
Date: 20250808

ACTIVE INGREDIENTS: SODIUM FLUORIDE 0.15 g/100 g; POTASSIUM NITRATE 5 g/100 g
INACTIVE INGREDIENTS: WATER; SACCHARIN SODIUM; SODIUM PHOSPHATE, TRIBASIC; SORBITOL; TITANIUM DIOXIDE; GLYCERIN; XANTHAN GUM; HYDRATED SILICA; SODIUM LAURYL SULFATE

5820184 Topco Max Str Sens Mint

Active ingredients / Purpose

Potassium nitrate 5%....................................................Antihypersensitivity

Sodium fluoride 0.24% (0.15% w/v fluoride ion)............Anticavity

Uses

aids in the prevention of dental cavities

WARNINGS

If pain/sensitivity still persists after 4 weeks of use, please visit your dentist. Stop use and see your doctor if the problem worsens. Sensitive teeth may indicate a serious problem that may need prompt care by a dentist.

Keep out of reach of children. If more than used for brushing is accidentally swallowed, get medical help or contact a Poison Control Center right away.

Directions

Adults and children 12 years of age and older: Apply at least a 1-inch strip of product onto a soft bristle toothbrush. Brush teeth thoroughly for at least one minute, preferably after each meal or at least twice a day (morning and evening) or as recommended by a dentist or physican. Make sure to brush all sensitive areas of the teeth.

DOSAGE AND ADMINISTRATION

Apply at least a 1-inch strip of the product onto a soft bristle toothbrush. Children under 12 years of age: consult a dentist or a doctor.

Other Information

Store in a cool dry place. Keep tube capped when not in use.

Inactive ingredients

cocamidopropyl betaine, flavor, glycerin, hydrated silica, PEG-8, sodium hydroxide, sodium methyl cocoyl taurate, sodium saccharin, sodium tripolyphosphate, sorbitol, titanium dioxide, water, xanthan gum